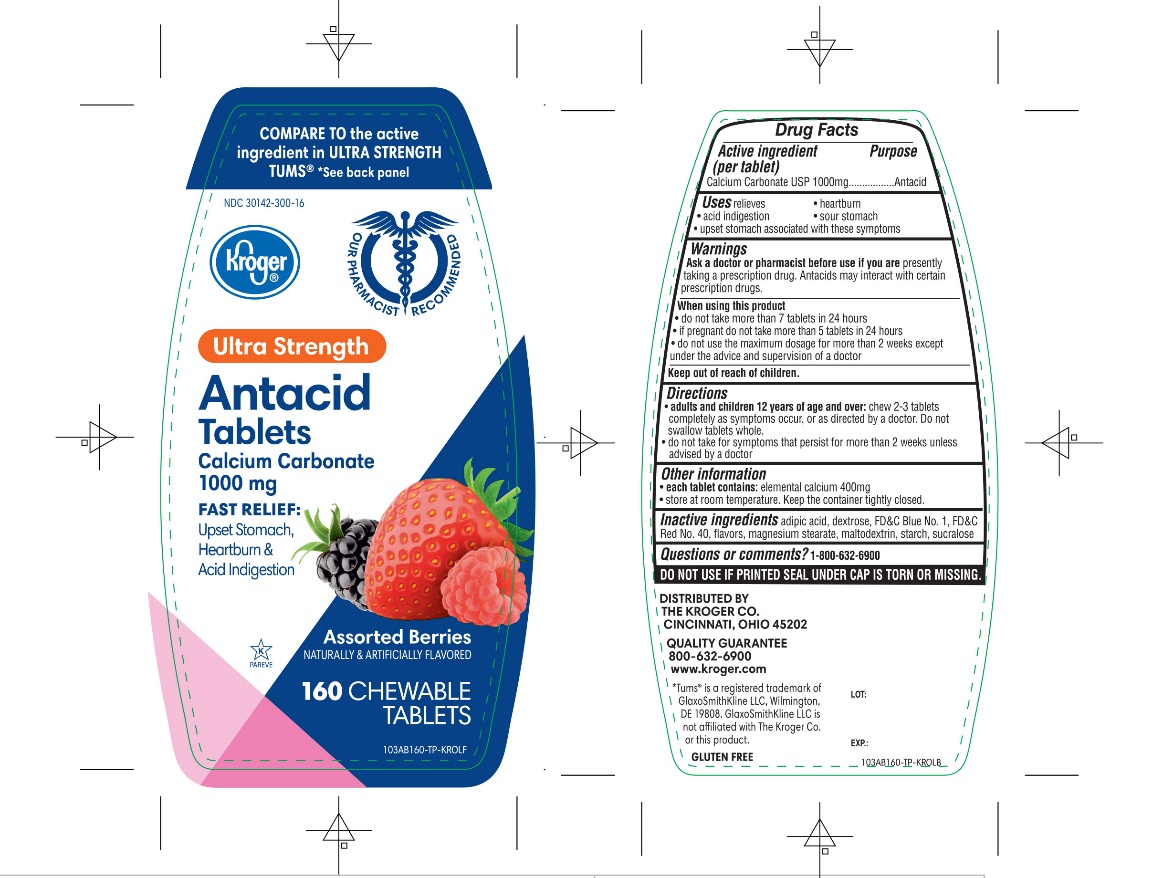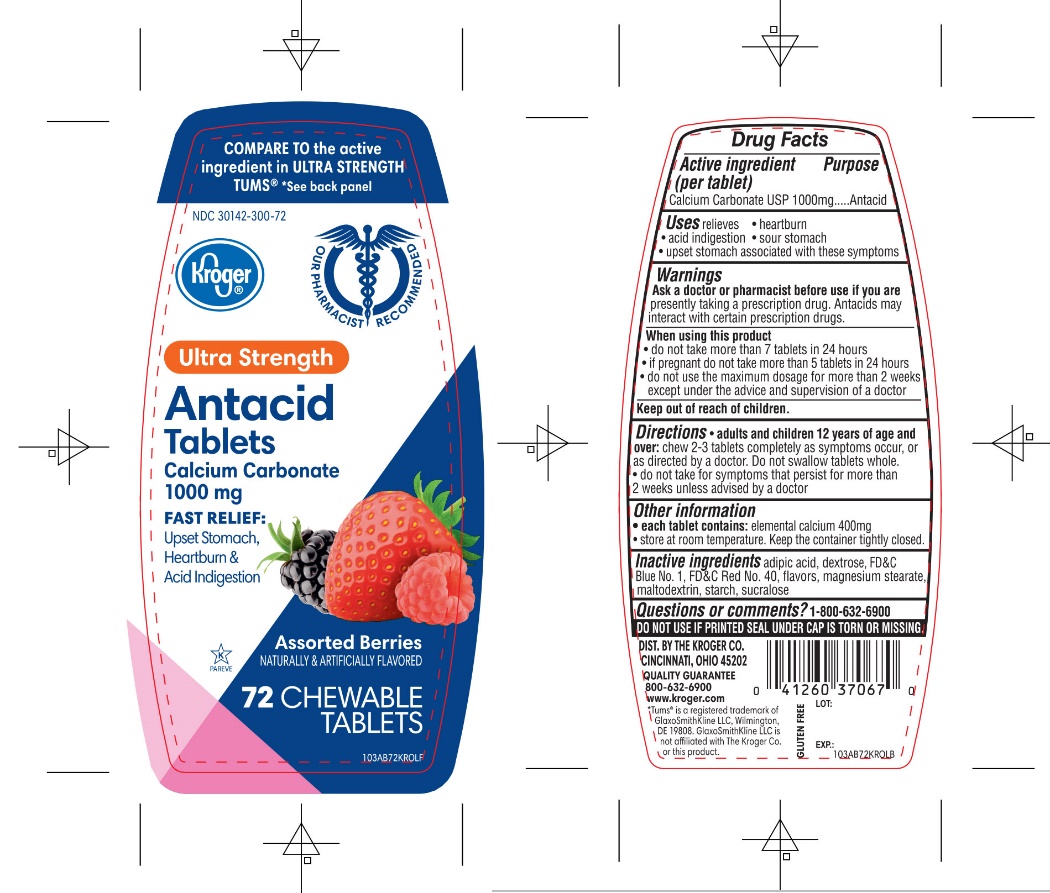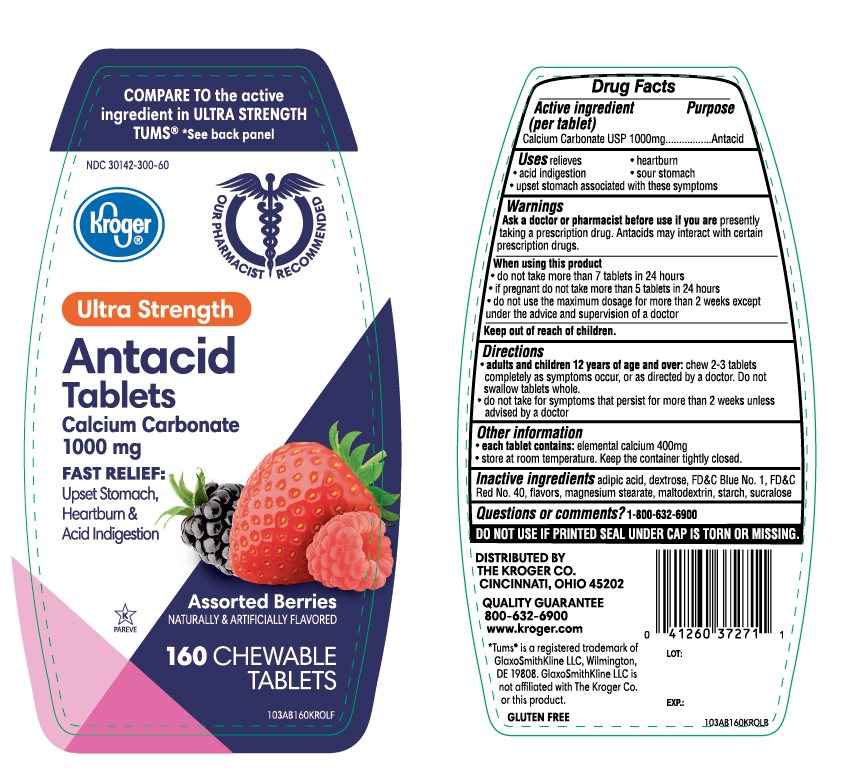 DRUG LABEL: Kroger Ultra Strength

NDC: 30142-300 | Form: TABLET, CHEWABLE
Manufacturer: KROGER COMPANY
Category: otc | Type: HUMAN OTC DRUG LABEL
Date: 20250813

ACTIVE INGREDIENTS: CALCIUM CARBONATE 1000 mg/1 1
INACTIVE INGREDIENTS: ADIPIC ACID; FD&C BLUE NO. 1; DEXTROSE, UNSPECIFIED FORM; MAGNESIUM STEARATE; MALTODEXTRIN; FD&C RED NO. 40; STARCH, CORN; SUCRALOSE

Kroger Ultra Strength Antacid Calcium Carbonate Drug Facts

Active ingredient (per tablet)

Calcium Carbonate USP 1000mg

Purpose

Antacid

Uses

relieves

- heartburn
- acid indigestion
- sour stomach
- upset stomach associated with these symptoms

Ask a doctor or pharmacist before use if you are

presently taking a prescription drug. Antacids may interact with certain prescription drugs.

When using this product

- do not take more than 7 tablets in 24 hours
- if pregnant do not take more than 5 tablets in 24 hours
- do not use the maximum dosage for more than 2 weeks except under the advice and supervision of a doctor

Directions

- adults and children 12 years of age and over:chew 2-3 tablets as symptoms occur, or as directed by a doctor
- do not take for symptoms that persist for more than 2 weeks unless advised by a doctor

Other information

- each tablet contains: elemental calcium 400mg
- Store below 30°C (86°F)
- Keep the container tightly closed
- For calcium and magnesium content see Supplement Facts.

Inactive ingredients

adipic acid, blue 1 lake, dextrose, flavors, magnesium stearate, red 40 lake, maltodextrin, starch, sucralose.

Questions or comments?

1-800-632-6900

Safety Sealed:

Do not use if printed seal under cap is torn or missing

Package/Label Principal Display Panel

Kroger®

COMPARE TO the active ingredient of TUMS®ULTRA STRENGTH

*See back panel

FAST RELIEF OF UPSET STOMACH, HEARTBURN, AND ACID INDIGESTION

ULTRA STRENGTH

Antacid Tablets

CALCIUM CARBONATE 1000 mg

Assorted Berry Flavors

GLUTEN FREE

Our Pharmacists Recommend

K PAREVE

DISTRIBUTED BY THE KROGER CO., CINCINNATI, OHIO 45202

QUALITY GUARANTEE

800-632-6900

www.kroger.com

*TUMS® IS A REGISTERED TRADEMARK OF GLAXOSMITHKLINE LLC, WILMINGTON, DE 19808. GLAXOSMITHKLINE LLC IS NOT AFFILIATED WITH THE KROGER CO. OR THIS PRODUCT.

Package Label 160 Chewable Tablets

Generic Section

Package Label for 72 Chewable Tablets

Generic Section

Package Label for 160 Twin Pack Chewable Tablets